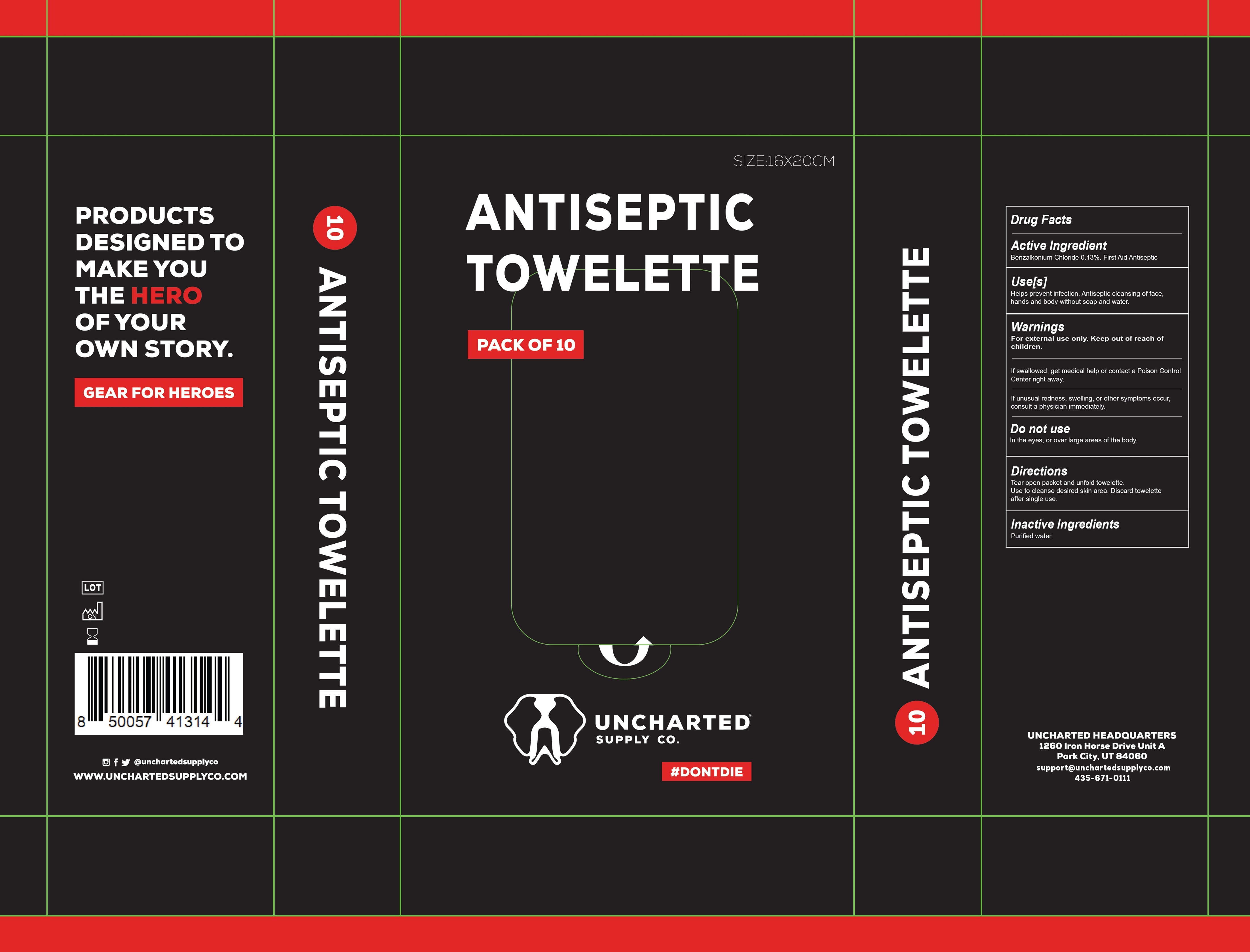 DRUG LABEL: Antiseptic Towelette
NDC: 82264-008 | Form: CLOTH
Manufacturer: UNCHARTED SUPPLY COMPANY, INC.
Category: otc | Type: HUMAN OTC DRUG LABEL
Date: 20241114

ACTIVE INGREDIENTS: BENZALKONIUM CHLORIDE 1.3 mg/1 g
INACTIVE INGREDIENTS: WATER

Antiseptic Towelette

Active lngredient

Benzalkonium Chloride 0.13%.

PURPOSE

First Aid Antiseptic

Use[s]

Helps prevent infection. Antiseptic cleansing of face, hands and body without soap and water.

Warnings

For external use only.

Keep out of reach of children.

If swallowed, get medical help or contact a Poison Control Center right away.

If unusual redness, swelling, or other symptoms occur, consult a physician immediately.

Do not use

In the eyes, or over large areas of the body.

Directions

Tear open packet and unfold towelette. Use to cleanse desired skin area. Discard towelette after single use.

Inactive Ingredients

Purified water.